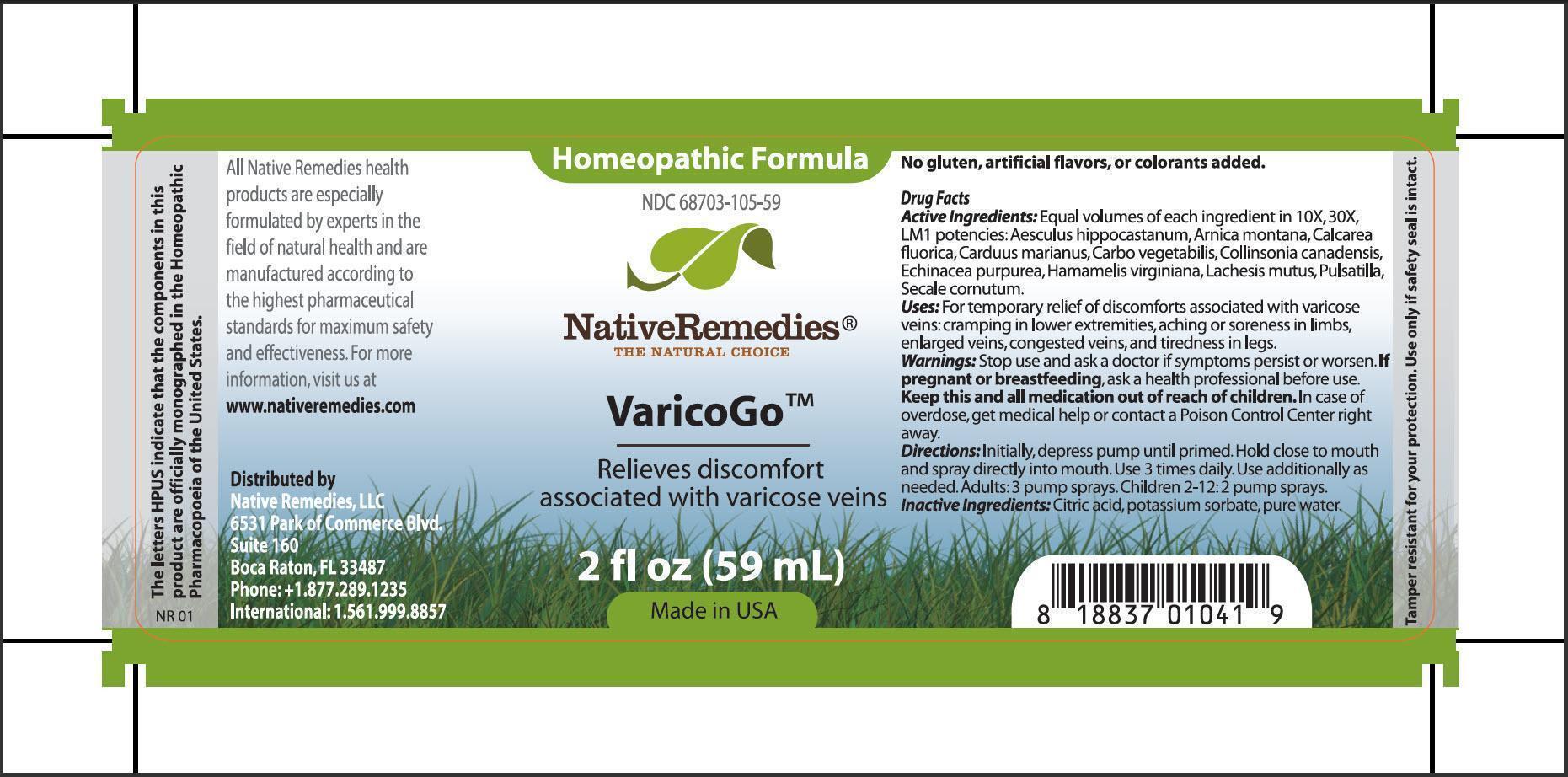 DRUG LABEL: VaricoGo
NDC: 68703-105 | Form: SPRAY
Manufacturer: Native Remedies, LLC
Category: homeopathic | Type: HUMAN OTC DRUG LABEL
Date: 20130626

ACTIVE INGREDIENTS: HORSE CHESTNUT 10 [hp_X]/59 mL; ARNICA MONTANA 10 [hp_X]/59 mL; CALCIUM FLUORIDE 10 [hp_X]/59 mL; ACTIVATED CHARCOAL 10 [hp_X]/59 mL; SILYBUM MARIANUM SEED 10 [hp_X]/59 mL; COLLINSONIA CANADENSIS ROOT 10 [hp_X]/59 mL; ECHINACEA PURPUREA 10 [hp_X]/59 mL; HAMAMELIS VIRGINIANA ROOT BARK/STEM BARK 10 [hp_X]/59 mL; LACHESIS MUTA VENOM 10 [hp_X]/59 mL; PULSATILLA VULGARIS 10 [hp_X]/59 mL; CLAVICEPS PURPUREA SCLEROTIUM 10 [hp_X]/59 mL
INACTIVE INGREDIENTS: CITRIC ACID MONOHYDRATE; POTASSIUM SORBATE; WATER

VaricoGo

PURPOSE

Relieves discomfort associated with varicose veins

Drug Facts
Active Ingredients: Equal volumes of each ingredient in 10X, 30X, LM10 potencies: Aesculus hippocastanum, Arnica montana, Calcarea fluorica, Carduus marianus, Carbo vegetabilis, Collinsonia canadensis, Echinacea purpurea, Hamamelis virginiana, Lachesis mutus, Pulsatilla, Secale cornutum

INDICATIONS AND USAGE

Uses: For temporary relief of discomforts associated with varicose veins: cramping in lower extremities, aching or soreness in limbs, enlarged veins, congested veins, and tiredness in legs

WARNINGS

Warnings: Stop use and ask a doctor if symptoms persist or worsen

PREGNANCY OR BREAST FEEDING

If pregnant or breastfeeding, ask a health professional before use

KEEP OUT OF REACH OF CHILDREN

Keep this and all medication out of reach of children

OVERDOSAGE

In case of overdose, get medical help or contact a Poison Control Center right away

DOSAGE AND ADMINISTRATION

Directions: Initially, depress pump until primed. Hold close to mouth and spray directly into mouth. Use 3 times daily. Use additionally as needed. Adults: 3 pump sprays. Children 2-12: 2 pump sprays

Inactive Ingredients: Citric acid, potassium sorbate, pure water

PATIENT COUNSELING INFORMATION

The lleters HPUS indicate that the components in this product are officially monographed in the Homeopathic Pharmacopoeia of the United States.

All Native Remedies health products are especially formulated by experts in the field of natural health and are manufactured according to the highest pharmaceutical standards for maximum safety and effectiveness. For more information, visit us at www.nativeremedies.com

Distributed by
Native Remedies, LLC
6531 Park of Commerce Blvd.
Suite 160
Boca Raton, FL 33487
Phone:+1.877.289.1235
International:1.561.999.8857

No gluten, artificial flavors, or colorants added

STORAGE AND HANDLING

Tamper resistant for your protection. Use only if safety seal is intact